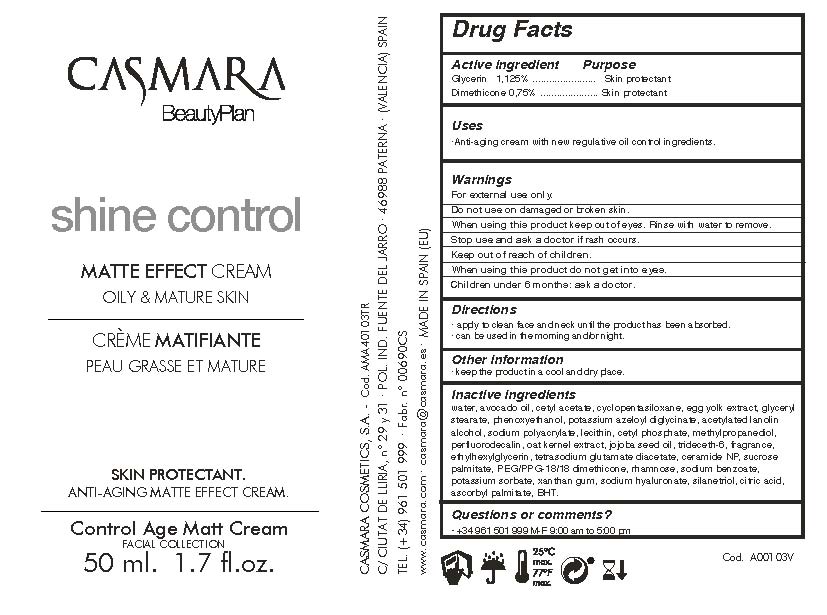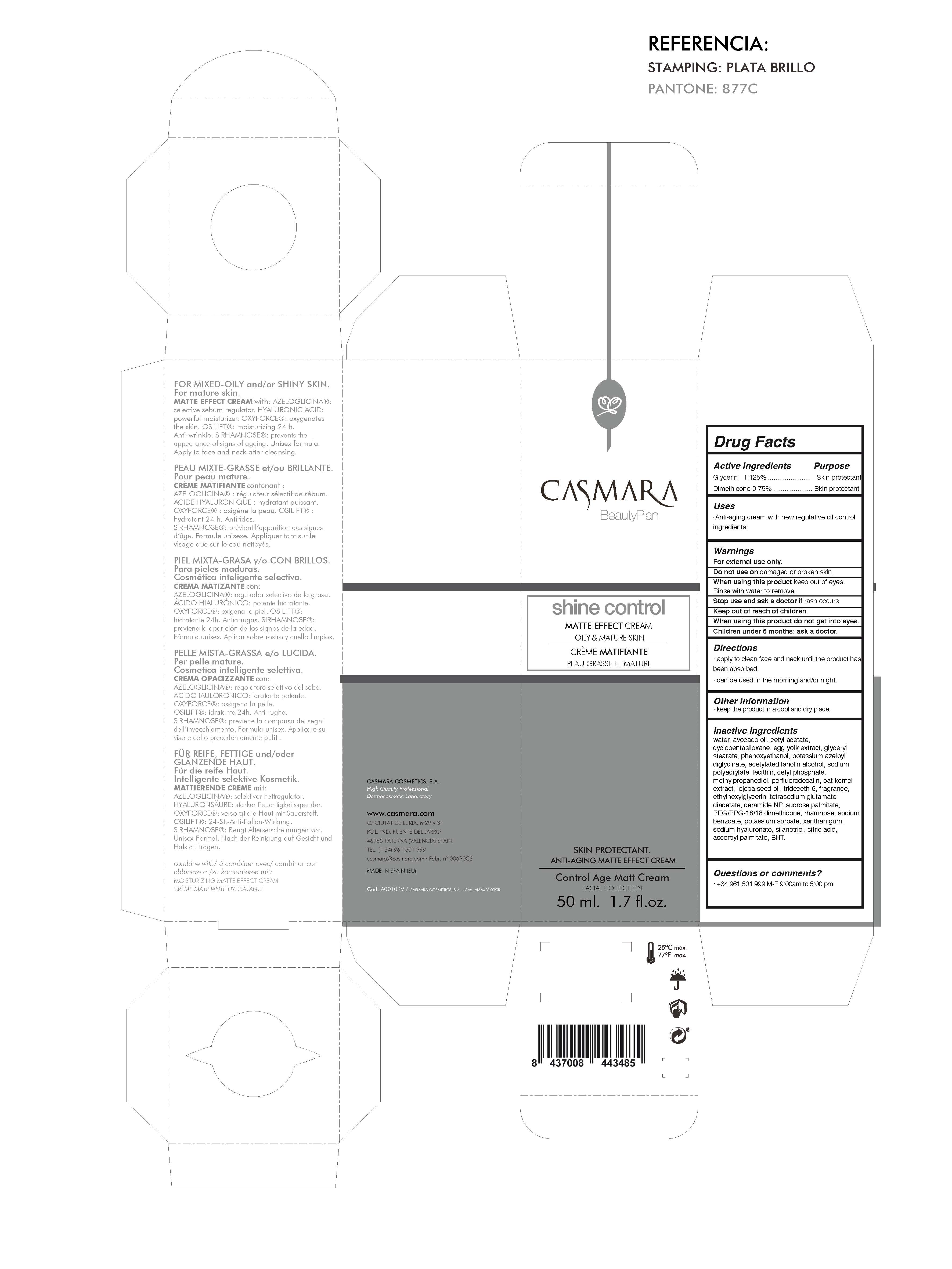 DRUG LABEL: Shine Control Matte Effect Cream
NDC: 20151-096 | Form: CREAM
Manufacturer: CASMARA COSMETICS, SA
Category: otc | Type: HUMAN OTC DRUG LABEL
Date: 20170226

ACTIVE INGREDIENTS: GLYCERIN 1.12 mg/1 mL; DIMETHICONE 0.75 mg/1 mL
INACTIVE INGREDIENTS: SODIUM BENZOATE 0.01 mg/1 mL; ACETYLATED LANOLIN ALCOHOLS 0.78 mg/1 mL; AVOCADO OIL 6 mg/1 mL; POTASSIUM SORBATE 0.016 mg/1 mL; CYCLOMETHICONE 5 4.22 mg/1 mL; WATER 71.25 mg/1 mL; CETYL ACETATE 5.22 mg/1 mL; EGG YOLK 2 mg/1 mL; METHYLPROPANEDIOL 0.6 mg/1 mL; GLYCERYL STEARATE SE 2 mg/1 mL; XANTHAN GUM 0.016 mg/1 mL; JOJOBA OIL 0.22 mg/1 mL; CITRIC ACID MONOHYDRATE 0.099 mg/1 mL; ETHYLHEXYLGLYCERIN 0.1 mg/1 mL; TETRASODIUM GLUTAMATE DIACETATE 0.094 mg/1 mL; SODIUM POLYACRYLATE (2500000 MW) 0.75 mg/1 mL; PERFLUNAFENE 0.52 mg/1 mL; PHENOXYETHANOL 0.93 mg/1 mL; HYDROGENATED SOYBEAN LECITHIN 0.62 mg/1 mL; HYDROLYZED JOJOBA ESTERS (POTASSIUM SALTS) 0.42 mg/1 mL; CETYL PHOSPHATE 0.62 mg/1 mL; POTASSIUM AZELOYL DIGLYCINATE 0.9 mg/1 mL; CERAMIDE NP 0.09 mg/1 mL; PEG/PPG-18/18 DIMETHICONE 0.09 mg/1 mL; HYALURONATE SODIUM 0.01 mg/1 mL; SILANETRIOL 0.009 mg/1 mL; ASCORBYL PALMITATE 0.0029 mg/1 mL; TRIDECETH-6 0.22 mg/1 mL; SUCROSE PALMITATE 0.09 mg/1 mL; RHAMNOSE 0.07 mg/1 mL; BUTYLATED HYDROXYTOLUENE 0.017 mg/1 mL

Shine Control
Matte Effect Cream
Oily Mature Cream

Active Ingredients Purpose

Glycerin 1.125%.................... Skin Protectant

Dimethicone 0.75%................Skin Protectant

Uses

. Anti aging cream with new regulative oil control ingredients

Uses

.Anti aging cream with new regulative oil control ingredients

Warnings

For external use only.

Do not use on damaged or broken skin.

When using this product keep our of the eyes. Rinse with water to remove.

Stop use and ask a doctor if rash occurs.

Keep out of reach of children.

Whhen using this product do not get into eyes.

Children under 6 months: as a doctor.

Keep out of reach of children.

Warnings

Stop use and ask a doctor if rash occurs.

Questions or comments?

(305) 777-0548 M-F 9:00 am to 5:00 pm

Directions

. apply to clean face and neck until the product has been absorbed

. can be used in the morning and/or night.

Other information

. keep the product in a cool and dry place.

Inactive ingredients

Water, Avocado oil, Cetyl acetate, Cyclopentasiloxane, Egg yolk extract, Glyceryl stearate, Phenoxyethanol, Potassium azeloyl diglycinate, Acetylated lanolin alcohol, Sodium polyacrylate, Lecithin, Cetyl phosphate, Methylpropanediol, Perfluorodecalin, Oat Kernel extract, Jojoba seed oil, Trideceth-6, Fragrance, Ethylhexylglycerin, Tetrasodium glutamate diacetate, Ceramide NP
Sucrose palmitate, PEG/PPG-18/18 dimethicone, Rhamnose, Sodium benzoate, Potassium sorbate, Xanthan gum, Sodium hyaluronate, Silanetriol, Citric acid, Ascorbyl palmitate, BHT

Directions

. apply to clean face and neck until the product has been absorbed

. can be used in the morning and/or night.